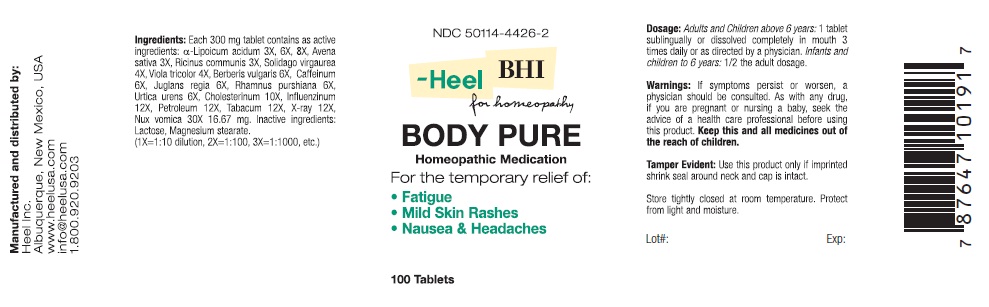 DRUG LABEL: Body Pure
NDC: 50114-4426 | Form: TABLET
Manufacturer: Heel Inc
Category: homeopathic | Type: HUMAN OTC DRUG LABEL
Date: 20120529

ACTIVE INGREDIENTS: .ALPHA.-LIPOIC ACID 3 [hp_X]/1 1; AVENA SATIVA FLOWERING TOP 3 [hp_X]/1 1; RICINUS COMMUNIS SEED 3 [hp_X]/1 1; SOLIDAGO VIRGAUREA FLOWERING TOP 4 [hp_X]/1 1; VIOLA TRICOLOR 4 [hp_X]/1 1; BERBERIS VULGARIS ROOT BARK 6 [hp_X]/1 1; CAFFEINE 6 [hp_X]/1 1; JUGLANS REGIA FLOWERING TOP 6 [hp_X]/1 1; FRANGULA PURSHIANA BARK 6 [hp_X]/1 1; URTICA URENS 6 [hp_X]/1 1; CHOLESTEROL 10 [hp_X]/1 1; INFLUENZA A VIRUS A/SINGAPORE/6/86 (H1N1) ANTIGEN (HEAT INACTIVATED) 12 [hp_X]/1 1; KEROSENE 12 [hp_Q]/1 1; TOBACCO LEAF 12 [hp_X]/1 1; ALCOHOL, X-RAY EXPOSED (1000 RAD) 12 [hp_X]/1 1; STRYCHNOS NUX-VOMICA SEED 30 [hp_X]/1 1
INACTIVE INGREDIENTS: LACTOSE; MAGNESIUM STEARATE

BODY PURE TABLET

KEEP OUT OF REACH OF CHILDREN

Keep this and all medicines out of the reach of children.

INDICATIONS AND USAGE

For the temporary relief of:

- Fatigue
- Mild Skin Rashes
- Nausea and Headaches

WARNINGS

If symptoms persist or worsen, a physician should be consulted. As with any drug, if you are pregnant or nursing a baby, seek the advise of a health care professional before using this product.

DOSAGE AND ADMINISTRATION

Adults and children above 6 years: 1 tablet sublingually or dissolved completely in mouth 3 times daily of as directed by a physician. Infants and children to 6 years: 1/2 the adult dosage.

ACTIVE INGREDIENT

Each 300mg tablet contains as active ingredients: a-Lipicum 3X, Avena saltvia 3X, Ricinus communis 3X, Solidago vigaurea 4X, Viola tricolor 4X, Berberis vulgaris 6X, Caffeinum 6X, Juglans regia 6X, Rhamus purshiana 6X, Urtica urens 6X, Cholesterium 10X, Influenzium 12X, Petroleum 12X, Tabacum 12X, X-ray 12X, Nux vomica 30x 16.67 mg

INACTIVE INGREDIENT

Inactive ingredients: Lactose, Magnesium Sterarate

PURPOSE

Fatigue, Mild Skin Rashes, Nausea, and Headaches